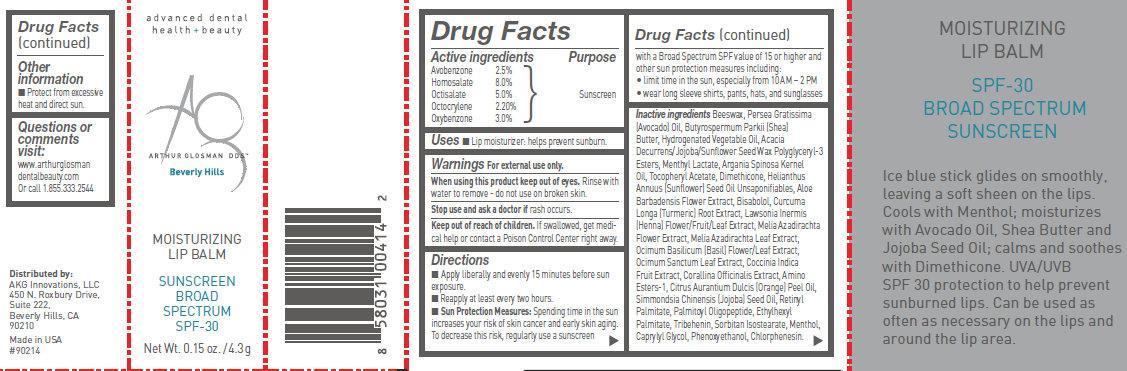 DRUG LABEL: Moisturizing Lip BalmSPF30
NDC: 62111-0211 | Form: STICK
Manufacturer: AKG Innovations LLC
Category: otc | Type: HUMAN OTC DRUG LABEL
Date: 20140213

ACTIVE INGREDIENTS: AVOBENZONE 25 mg/1 g; HOMOSALATE 80 mg/1 g; OCTISALATE 50 mg/1 g; OCTOCRYLENE 22.0 mg/1 g; OXYBENZONE 30 mg/1 g
INACTIVE INGREDIENTS: YELLOW WAX; AVOCADO OIL; SHEA BUTTER; MENTHYL LACTATE, (-)-; ARGAN OIL; .ALPHA.-TOCOPHEROL ACETATE; DIMETHICONE; SUNFLOWER OIL; ALOE VERA FLOWER; LEVOMENOL; CURCUMA LONGA LEAF; LAWSONIA INERMIS FLOWERING TOP; AZADIRACHTA INDICA FLOWER; AZADIRACHTA INDICA LEAF; OCIMUM BASILICUM FLOWERING TOP; OCIMUM TENUIFLORUM TOP; COCCINIA GRANDIS FRUIT; CORALLINA OFFICINALIS; CITRUS SINENSIS FLOWER OIL; JOJOBA OIL; VITAMIN A PALMITATE; PALMITOYL OLIGOPEPTIDE; ETHYLHEXYL PALMITATE; TRIBEHENIN; Sorbitan Isostearate; MENTHOL; CAPRYLYL GLYCOL; PHENOXYETHANOL; CHLORPHENESIN

MOISTURIZING LIP BALM SPF30

Active ingredients

Avobenzone 2.5%

Homosalate 8.0%

Octisalate 5.0%

Octocrylene 2.20%

Oxybenzone 3.0%

Purpose

Sunscreen

Uses

■Lip moisturizer: helps prevent sunburn.

Warnings

For external use only

When using this product keep out of eyes.

Rinse with water to remove - do not use on broken skin.

Keep out of reach of children.

If swallowed, get medical help or contact a Poison Control Center right away.

Directions

■Apply liberally and evenly 15 minutes before sun exposure.

■Reapply at least every two hours.

■Sun Protection Measures: Spending time in the sun increases

your risk of skin cancer and early skin aging. To decrease this risk,

regularly use a sunscreen with a Broad Spectrum SPF value of 15

or higher and other sun protection measures including:

• limit time in the sun, especially from 10 AM – 2 PM

• wear long sleeve shirts, pants, hats, and sunglasses

Inactive ingredients

Beeswax, Persea Gratissima

(Avocado) Oil, Butyrospermum Parkii (Shea)

Butter, Hydrogenated Vegetable Oil, Acacia

Decurrens/Jojoba/Sunflower Seed Wax Polyglyceryl-3

Esters, Menthyl Lactate, Argania Spinosa Kernel

Oil, Tocopheryl Acetate, Dimethicone, Helianthus

Annuus (Sunflower) Seed Oil Unsaponifiables, Aloe

Barbadensis Flower Extract, Bisabolol, Curcuma

Longa (Turmeric) Root Extract, Lawsonia Inermis

(Henna) Flower/Fruit/Leaf Extract, Melia Azadirachta

Flower Extract, Melia Azadirachta Leaf Extract,

Ocimum Basilicum (Basil) Flower/Leaf Extract,

Ocimum Sanctum Leaf Extract, Coccinia Indica

Fruit Extract, Corallina Officinalis Extract, Amino

Esters-1, Citrus Aurantium Dulcis (Orange) Peel Oil,

Simmondsia Chinensis (Jojoba) Seed Oil, Retinyl

Palmitate, Palmitoyl Oligopeptide, Ethylhexyl

Palmitate, Tribehenin, Sorbitan Isostearate, Menthol,

Caprylyl Glycol, Phenoxyethanol, Chlorphenesin.

Other information

■Protect from excessive heat and direct sun.

Questions or comments visit:

www.arthurglosmandentalbeauty.com

Or call 1.855.333.2544

MOISTURIZING LIP BALM SUNSCREEN BROAD SPECTRUM SPF-30 (62111-0211-3)

advanced dental health - beauty

ARTHUR GLOSMAN DDS

Beverly Hills

MOISTURIZING

LIP BALM

SUNSCREEN

BROAD

SPECTRUM

SPF-30

Net Wt. 0.15 oz. / 4.3 g

Distributed by:

AKG Innovations, LLC

450 N. Roxbury Drive,

Suite 222,

Beverly Hills, CA

90210

Made in USA

#90213

MOISTURIZING

LIP BALM

SPF-30

BROAD SPECTRUM

SUNSCREEN

Ice blue stick glides on smoothly,

leaving a soft sheen on the lips.

Cools with Menthol; moisturizes

with Avocado Oil, Shea Butter and

Jojoba Seed Oil; calms and soothes

with Dimethicone. UVA/UVB

SPF 30 protection to help prevent

sunburned lips. Can be used as

often as necessary on the lips and

around the lip area.